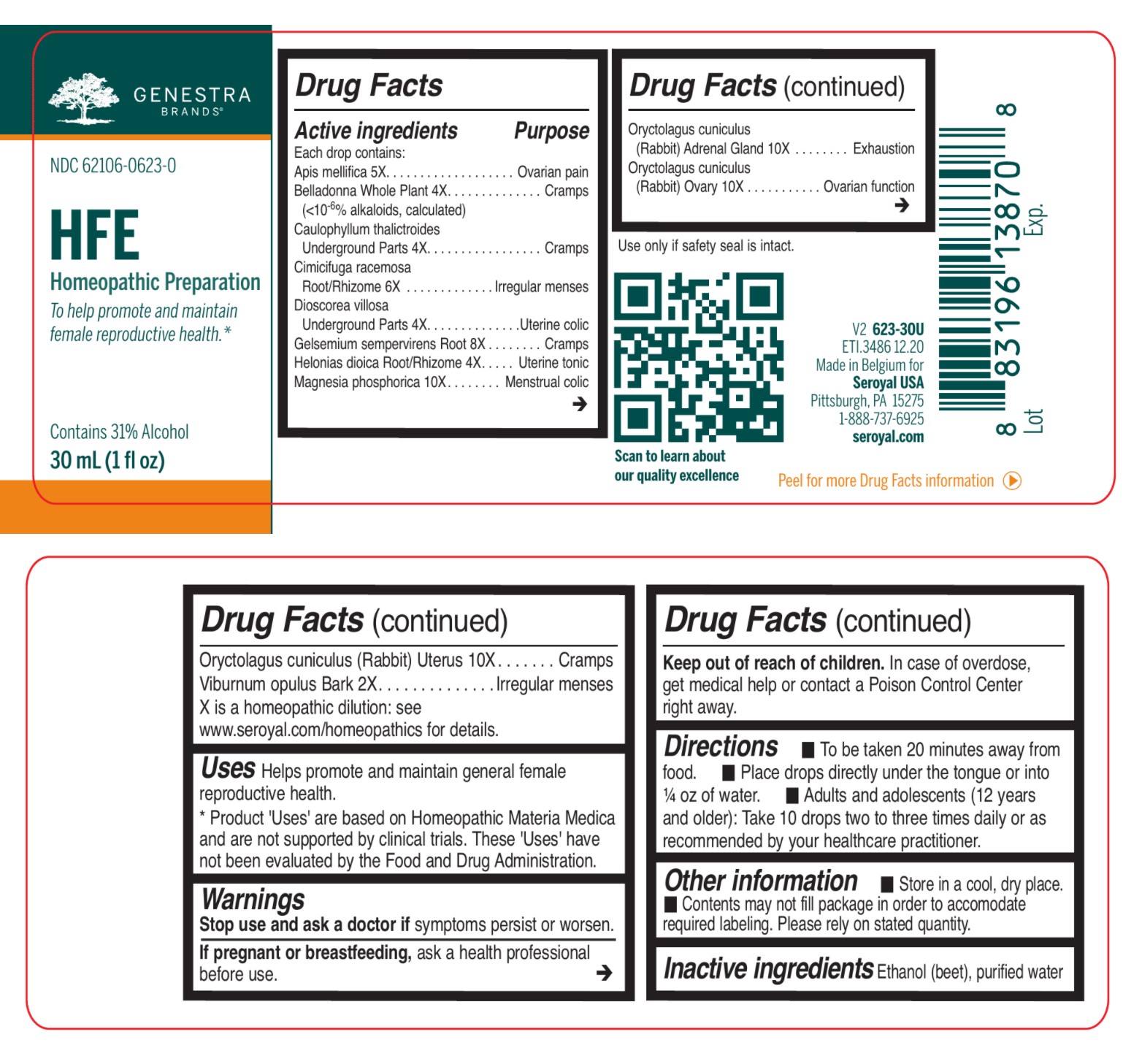 DRUG LABEL: HFE
NDC: 62106-0623 | Form: LIQUID
Manufacturer: Seroyal USA
Category: homeopathic | Type: HUMAN OTC DRUG LABEL
Date: 20210722

ACTIVE INGREDIENTS: DIOSCOREA VILLOSA ROOT 4 [hp_X]/30 mL; ORYCTOLAGUS CUNICULUS OVARY 10 [hp_X]/30 mL; APIS MELLIFERA 5 [hp_X]/30 mL; ATROPA BELLADONNA 4 [hp_X]/30 mL; BLACK COHOSH 6 [hp_X]/30 mL; CAULOPHYLLUM THALICTROIDES ROOT 4 [hp_X]/30 mL; CHAMAELIRIUM LUTEUM ROOT 4 [hp_X]/30 mL; ORYCTOLAGUS CUNICULUS ADRENAL GLAND 10 [hp_X]/30 mL; VIBURNUM OPULUS BARK 2 [hp_X]/30 mL; GELSEMIUM SEMPERVIRENS ROOT 8 [hp_X]/30 mL; MAGNESIUM PHOSPHATE, DIBASIC TRIHYDRATE 10 [hp_X]/30 mL; ORYCTOLAGUS CUNICULUS UTERUS 10 [hp_X]/30 mL
INACTIVE INGREDIENTS: WATER; ALCOHOL

HFE

Active ingredients
Each drop contains:
Apis mellifica 5X
Belladonna Whole Plant 4X
(< 10-6 % alkaloids, calculated)
Caulophyllum thalictroides Underground Parts 4X
Cimicifuga racemosa Root/Rhizome 6X
Dioscorea villosa Underground Parts 4X
Gelsemium sempervirens Root 8X
Helonias dioica Root/Rhizome 4X
Magnesia phosphorica 10X

Oryctolagus cuniculus (Rabbit) Adrenal Gland 10X
Oryctolagus cuniculus (Rabbit) Ovary 10X

Oryctolagus cuniculus (Rabbit) Uterus 10X
Viburnum opulus Bark 2X

Uses

Helps promote and maintain general female reproductive health.
Product 'Uses' are based on Homeopathic Materia Medica and have not been clinically tested. These 'Uses' have not been evaluated by the Food and Drug Administration.

Warnings
Stop use and ask a doctor if symptoms persist or worsen.
If pregnant or breastfeeding, ask a health professional before use.

Keep out of reach of children. In case of overdose, get medical help or contact a Poison Control Center right away.

Keep out of reach of children.

PREGNANCY OR BREAST FEEDING

If pregnant or breastfeeding, ask a health professional before use.

OVERDOSAGE

In case of overdose, get medical help or contact a Poison Control Center right away.

Stop use and ask a doctor if symptoms persist or worsen.

Other information

Store in a cool, dry place.

Use only if safety seal is intact

Contents may not fill package in order to accomodate required labelling. Please rely on stated quantity.

Inactive ingredients

Ethanol (beet), purified water

Directions

To be taken 20 minutes away from food. Place drops directly under the tongue or into ¼ oz of water.

Adults and adolescents (12 years and older): Take 10 drops two to three times daily or as recommended by your healthcare practitioner.

Children (under 12 years): Take under the direction of your healthcare practitioner.

Uses

Helps promote and maintain general female reproductive health.
Product 'Uses' are based on Homeopathic Materia Medica and have not been clinically tested. These 'Uses' have not been evaluated by the Food and Drug Administration.

Directions

To be taken 20 minutes away from food. Place drops directly under the tongue or into ¼ oz of water.

Adults and adolescents (12 years and older): Take 10 drops two to three times daily or as recommended by your healthcare practitioner.

Children (under 12 years): Take under the direction of your healthcare practitioner.

PACKAGE LABEL

NDC 62106-0623-0

HFE

HOMEOPATHIC PREPARATION

To help promote and maintain
female reproductive health.

Contains 31% Alcohol

1 fl oz (30 mL)